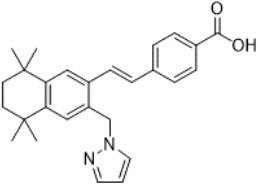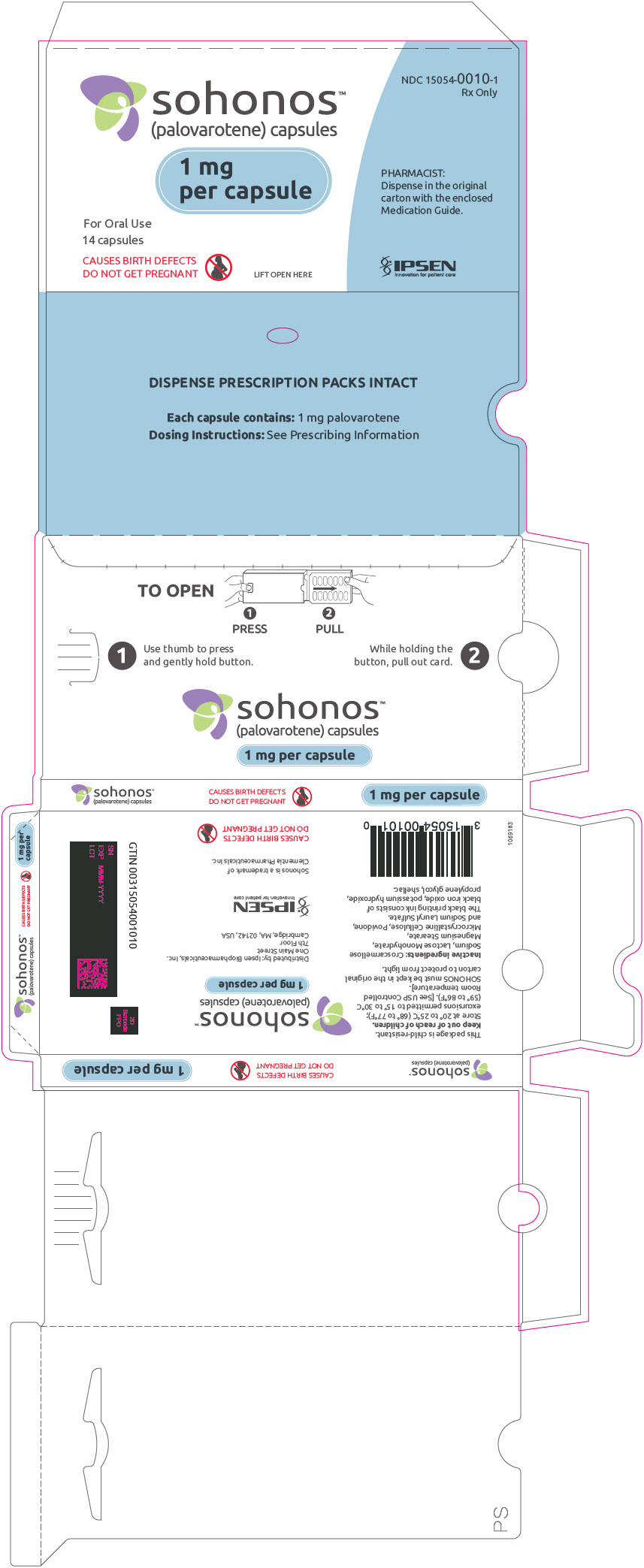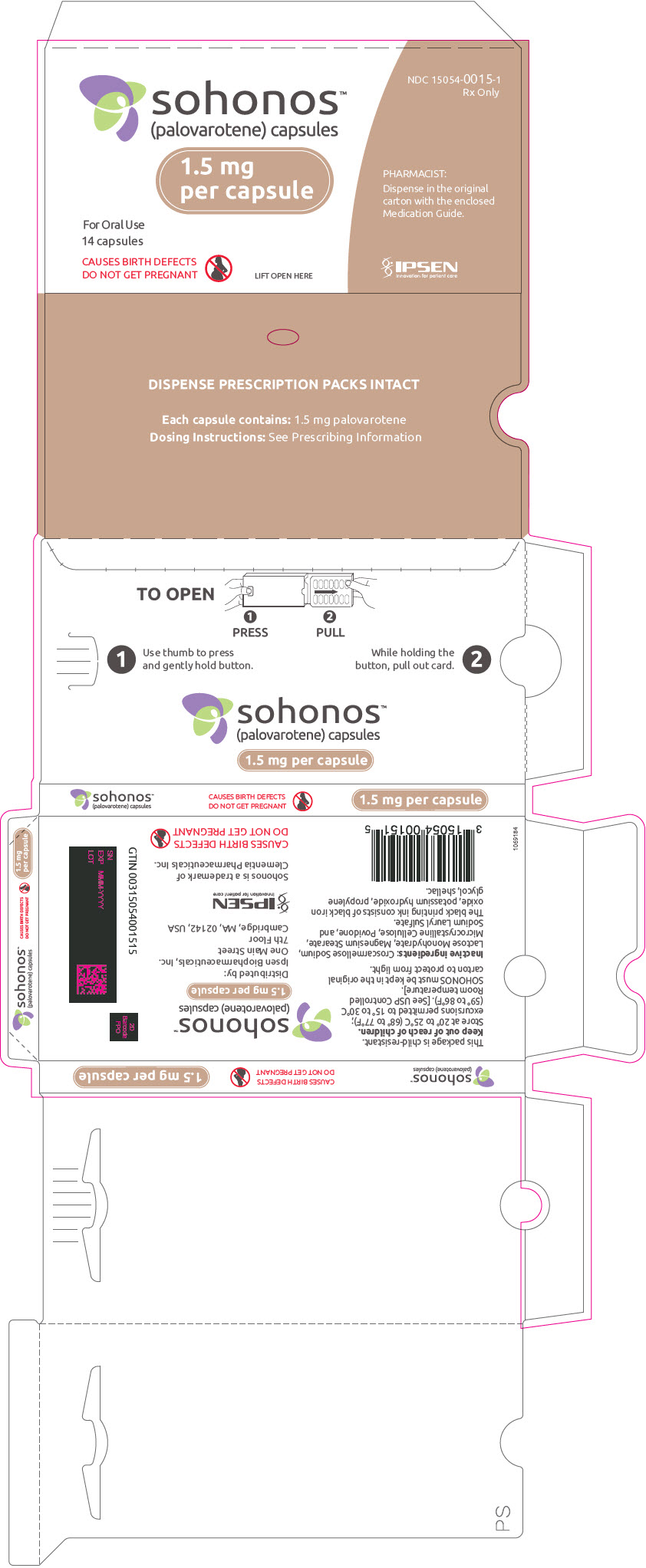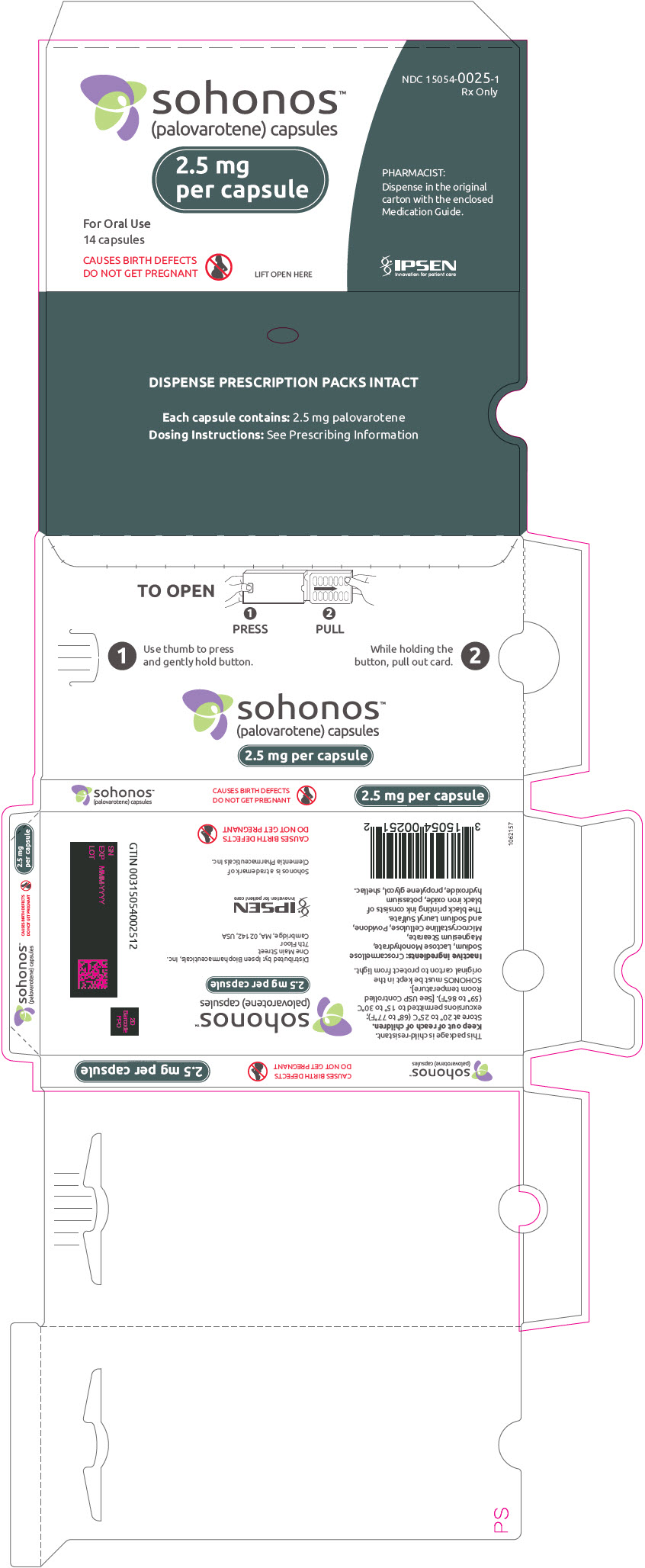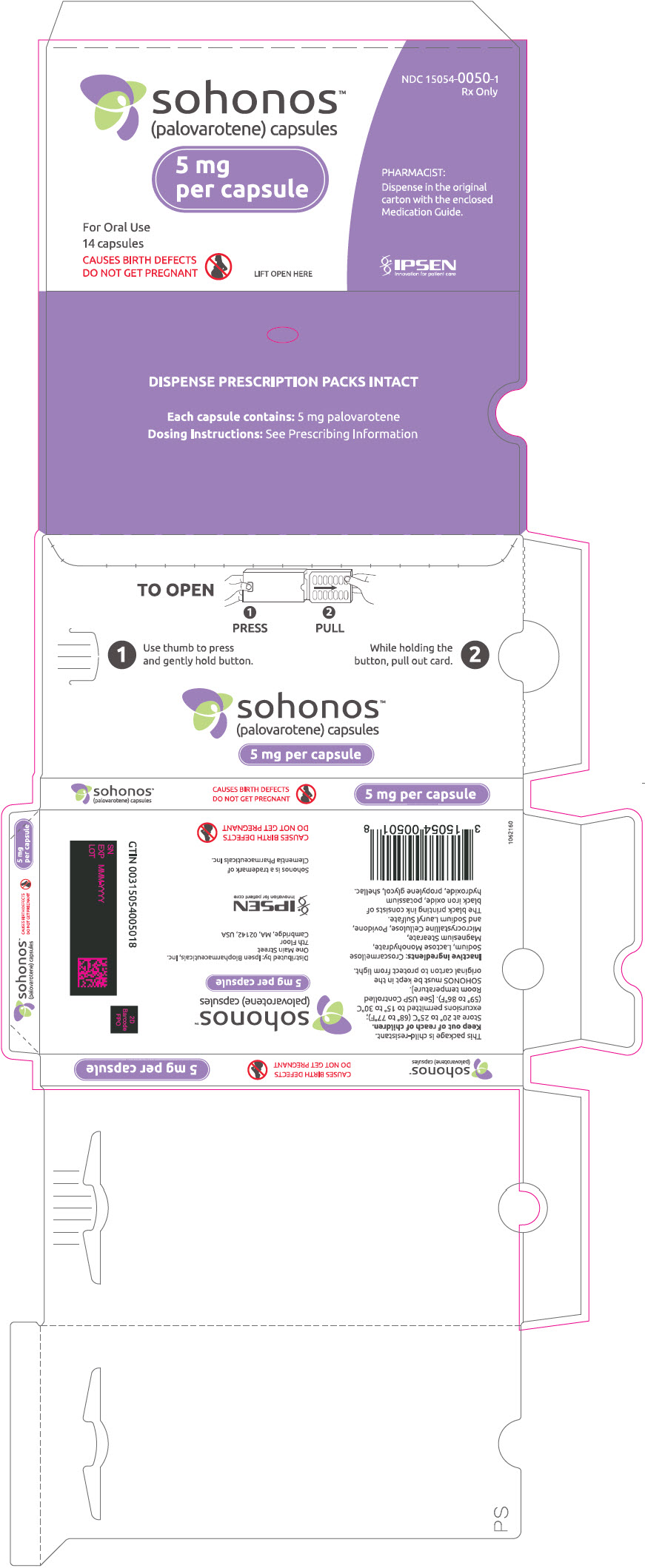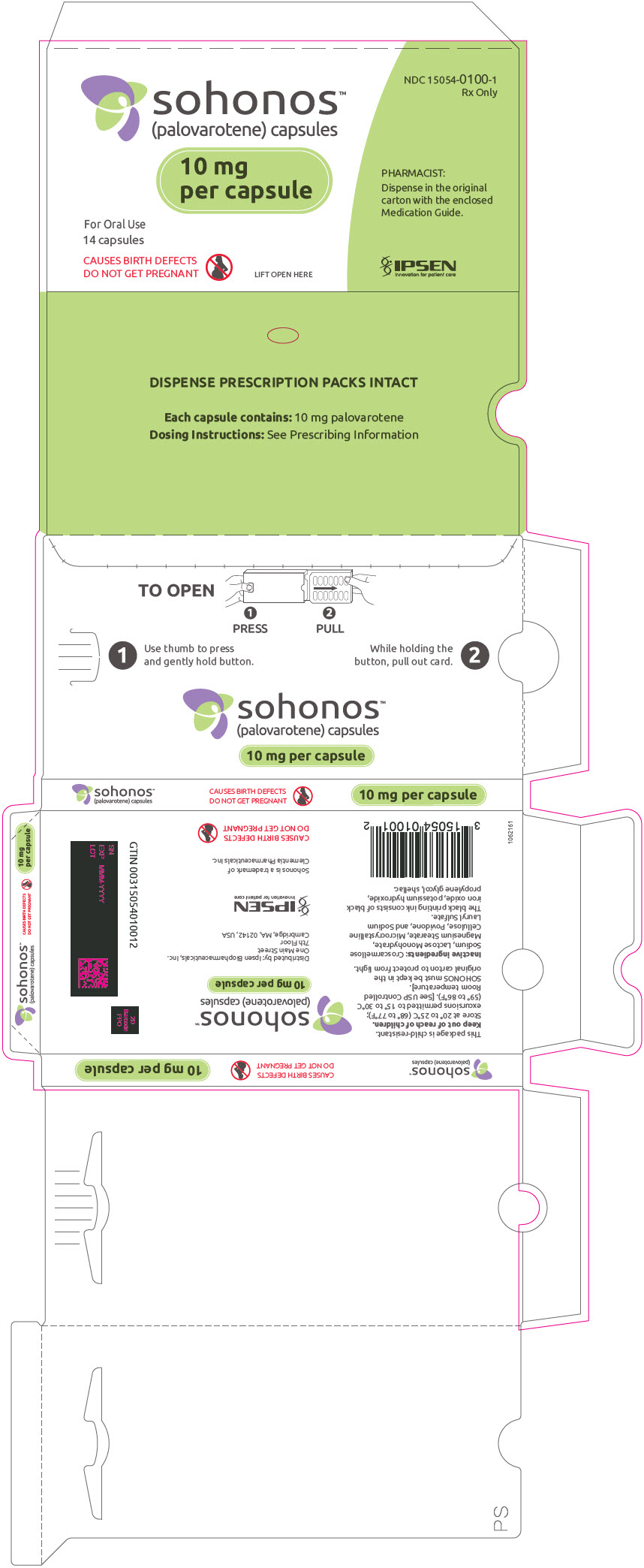 DRUG LABEL: SOHONOS
NDC: 15054-0010 | Form: CAPSULE
Manufacturer: Ipsen Biopharmaceuticals, Inc.
Category: prescription | Type: HUMAN PRESCRIPTION DRUG LABEL
Date: 20250318

ACTIVE INGREDIENTS: palovarotene 1 mg/1 1
INACTIVE INGREDIENTS: croscarmellose sodium; lactose monohydrate; magnesium stearate; microcrystalline cellulose; POVIDONE, UNSPECIFIED; sodium lauryl sulfate; GELATIN, UNSPECIFIED; Titanium Dioxide; FERROSOFERRIC OXIDE; POTASSIUM HYDROXIDE; propylene glycol; shellac

HIGHLIGHTS OF PRESCRIBING INFORMATION

These highlights do not include all the information needed to use SOHONOS® safely and effectively. See full prescribing information for SOHONOS.
SOHONOS (palovarotene) capsules, for oral use
Initial U.S. Approval: 2023

WARNING: EMBRYO-FETAL TOXICITY and PREMATURE EPIPHYSEAL CLOSURE IN GROWING PEDIATRIC PATIENTS

See full prescribing information for complete boxed warning.

- SOHONOS is contraindicated in pregnancy (5.1, 8.1) Because of the risk of teratogenicity and to minimize fetal exposure, SOHONOS is to be administered only if conditions for pregnancy prevention are met (5.1, 8.1)
- SOHONOS causes premature epiphyseal closure in growing pediatric patients with FOP, close monitoring is recommended (5.2, 8.4)

1 INDICATIONS AND USAGE

SOHONOS is a retinoid indicated for reduction in the volume of new heterotopic ossification in adults and children aged 8 years and older for females and 10 years and older for males with fibrodysplasia ossificans progressiva (FOP) (1).

2 DOSAGE AND ADMINISTRATION

- Obtain a negative pregnancy test in females of reproductive potential before initiation of SOHONOS (2.1)
- Recommended dosage includes a chronic daily dose, which can be increased for flare-up symptoms (2.2)
- For adults and pediatric patients 14 years and older: Recommended dosage is 5 mg once daily, with an increase in dose at the time of a flare-up to 20 mg once daily for 4 weeks, followed by 10 mg once daily for 8 weeks for a total of 12 weeks (20/10 mg flare-up treatment) (2.2)
- For pediatric patients under 14 years: Weight-adjusted for daily and flare-up dosing. Recommended daily dosage range from 2.5 to 5 mg. Refer to Table 1 in Full Prescribing Information for complete pediatric dosing (2.2)
- Take SOHONOS with food preferably at same time each day (2.3).
- Reduce the dose in the event of adverse reactions as appropriate (2.4)
- See Full Prescribing Information for complete dosing instructions (2)

3 DOSAGE FORMS AND STRENGTHS

Capsules: 1, 1.5, 2.5, 5, 10 mg (3)

4 CONTRAINDICATIONS

- Pregnancy (4, 5.1, 8.1)
- Hypersensitivity to retinoids or any component of SOHONOS (4, 11)

5 WARNINGS AND PRECAUTIONS

- Premature Epiphyseal Closure: Premature epiphyseal closure occurred with SOHONOS. Assess baseline skeletal maturity before SOHONOS therapy and monitor linear growth in growing pediatric patients (5.2)
- Mucocutaneous Adverse Reactions: Dry skin, lip dry, pruritus, rash, alopecia, erythema, skin exfoliation, and dry eye occurred with SOHONOS. Prevent or treat with skin emollients, sunscreen, artificial tears. Dosage reduction may be required in some patients (2.4, 5.3)
- Metabolic Bone Disorders: Decreased vertebral bone mineral content and bone density may occur. Assess for spinal fracture periodically using radiologic method (5.4)
- Psychiatric Disorders: Depression, anxiety, mood alterations and suicidal thoughts and behaviors occurred with SOHONOS. Contact healthcare provider if new or worsening symptoms develop in patients treated with SOHONOS (5.5)
- Night Blindness: May occur and make driving at night hazardous (5.6)

6 ADVERSE REACTIONS

Most common adverse reactions (incidence ≥10%) are dry skin, lip dry, arthralgia, pruritus, pain in extremity, rash, alopecia, erythema, headache, back pain, skin exfoliation, nausea, musculoskeletal pain, myalgia, dry eye, hypersensitivity, peripheral edema, and fatigue (6.1)

To report SUSPECTED ADVERSE REACTIONS, contact IPSEN Biopharmaceuticals, Inc at 1-855-463-5127 or FDA at 1-800-FDA-1088 or www.fda.gov/medwatch.

7 DRUG INTERACTIONS

- CYP3A4 Inhibitors: May increase SOHONOS exposure. Avoid concomitant use of strong/moderate CYP3A4 inhibitors. If concomitant use of moderate CYP3A4 inhibitors is unavoidable, reduce the dose of SOHONOS by half (2.5, 7.1)
- CYP3A4 Inducers: May decrease SOHONOS exposure. Avoid concomitant use of strong/moderate CYP3A4 inducers (7.1)
- Vitamin A: May cause additive effects (7.2)
- Tetracyclines: Avoid concomitant use with SOHONOS (7.3)
- Systemic Corticosteroids: No clinically significant drug interaction is expected with concomitant use of SOHONOS (7.4)

8 USE IN SPECIFIC POPULATIONS

- Pregnancy: May cause fetal harm (2.1, 4, 8.1)
- Growing pediatric patients are recommended to undergo baseline assessment of growth and skeletal maturity before starting treatment and continued clinical and radiographic monitoring every 6 to 12 months until patients reach skeletal maturity or final adult height (5.2, 8.4)

FULL PRESCRIBING INFORMATION

WARNING: EMBRYO-FETAL TOXICITY and PREMATURE EPIPHYSEAL CLOSURE IN GROWING PEDIATRIC PATIENTS

Embryo-Fetal Toxicity

SOHONOS is contraindicated in pregnancy. SOHONOS may cause fetal harm. Because of the risk of teratogenicity and to minimize fetal exposure, SOHONOS is to be administered only if conditions for pregnancy prevention are met [see Warnings and Precautions (5.1) and Use in Specific Populations (8.1)].

Premature Epiphyseal Closure

Premature epiphyseal closure occurs in growing pediatric patients treated with SOHONOS, close monitoring is recommended [see Warnings and Precautions (5.2) and Use in Specific Populations (8.4)].

1 INDICATIONS AND USAGE

SOHONOS is indicated for the reduction in volume of new heterotopic ossification in adults and pediatric patients aged 8 years and older for females and 10 years and older for males with fibrodysplasia ossificans progressiva (FOP).

2 DOSAGE AND ADMINISTRATION

2.1 Pregnancy Testing Prior to Treatment with SOHONOS

For females of reproductive potential, obtain a negative pregnancy test within one week prior to initiating and periodically during SOHONOS therapy. If pregnancy occurs, stop SOHONOS treatment immediately and refer patient to an obstetrician/gynecologist experienced in reproductive toxicity. [see Warnings and Precautions (5.1) and Use in Specific Populations (8.1, 8.3)].

2.2 Recommended Dosage and Duration

Dosage Overview

Take SOHONOS with food preferably at the same time each day [see Dosage and Administration (2.3)]. The recommended dosing for SOHONOS includes a chronic daily dosage (daily dose) which can then be modified/increased in the event of FOP flare-up symptoms (flare-up dose).

Initiate flare-up treatment at the onset of the first symptom indicative of a FOP flare-up or substantial high-risk traumatic event likely to lead to a flare-up (e.g., surgery, intramuscular immunization, mandibular blocks for dental procedures, muscle fatigue, blunt muscle trauma from bumps, bruises, falls, or influenza-like viral illnesses). Symptoms of a FOP flare-up typically include but are not limited to localized pain, soft tissue swelling/inflammation, redness, warmth, decreased joint range of motion, and stiffness.

Recommended Dosage for Adults and Pediatric Patients 14 Years and Older

- Daily Dose: The recommended SOHONOS daily dosage for adults and pediatric patients 14 years and older is 5 mg daily. Stop daily dosing when flare-up dosing begins.
- Flare-up Dose:
  - The recommended SOHONOS flare-up dosage for adults and pediatric patients 14 years and older is 20 mg daily for 4 weeks, followed by 10 mg daily for 8 weeks (for a total of 12 weeks of flare-up treatment), even if symptoms resolve earlier, then return to daily dosing of 5 mg.
  - If during the course of flare-up treatment, the patient experiences marked worsening of the original flare-up site or another flare-up at a new location, restart the 12-week flare-up dosing at 20 mg daily.
  - For flare-up symptoms that have not resolved at the end of the 12-week period, the 10 mg daily dosage may be extended in 4-week intervals and continued until the flare-up symptoms resolve. If new flare-up symptoms occur after the 5 mg daily dosing is resumed, flare-up dosing may be restarted.

Recommended Dosage for Pediatric Patients Aged 8 to 13 Years for Females and Aged 10 to 13 Years for Males

- Daily Dose: The recommended SOHONOS daily dosage for patients under 14 years of age is weight-based ranging from 2.5 mg to 5 mg daily (see Table 1). Stop daily dosing when flare-up dosing begins.
- Flare-up Dose:
  - The recommended flare-up SOHONOS dosage for patients under 14 years of age is weight-based (see Table 1). Administer the initial flare-up dosage once daily for 4 weeks, then administer the lower flare-up dosage once daily for 8 weeks (for a total of 12 weeks of flare-up treatment), even if symptoms resolve earlier, then return to daily dosing (see Table 1).
  - If during the course of flare-up treatment, the patient experiences marked worsening of the original flare-up site or another flare-up at a new location, restart the 12-week flare-up dosing with the Week 1 to 4 dose.
  - For flare-up symptoms that have not resolved at the end of the 12-week period, the Week 5 to 12 flare-up dose may be extended in 4-week intervals and continued until the flare-up symptoms resolve. If new flare-up symptoms occur after daily dosing is resumed, flare-up dosing may be restarted.

Table 1. Recommended SOHONOS Weight-Based Dosage for Pediatric Patients Aged 8 to 13 Years for Females and 10 to 13 Years for Males [once daily]
Weight | Daily Dosage | Week 1 to 4 Flare-up Dosage | Week 5 to 12 Flare-up Dosage
10 kg to 19.9 kg | 2.5 mg | 10 mg | 5 mg
20 kg to 39.9 kg | 3 mg | 12.5 mg | 6 mg
40 kg to 59.9 kg | 4 mg | 15 mg | 7.5 mg
≥ 60 kg | 5 mg | 20 mg | 10 mg

Missed Dose

If a dose of SOHONOS is missed, take the missed dose as soon as possible. If the dose has been missed by more than 6 hours, skip the missed dose, and continue with the next scheduled dose. Do not take two doses at the same time or in the same day.

2.3 Administration Instructions

Take SOHONOS with food preferably at the same time each day. SOHONOS may be swallowed whole, or capsules may be opened and the contents emptied onto one teaspoon (5 mL) of soft food (such as apple sauce, low-fat yogurt, or warm oatmeal) and taken within 1 hour of opening provided it was maintained at room temperature and not exposed to direct sunlight [see Clinical Pharmacology (12.3)]. Do not administer with grapefruit, pomelo, or juices containing these fruits.

2.4 Dosage Reduction for Adverse Reactions

If patients experience adverse reactions that require dosage reduction during either the SOHONOS daily dosing or flare-up dosing, reduce the daily dosage to the next lower dose as shown in Table 2 at the discretion of the healthcare provider; reduce the dosage further if adverse reactions do not improve. If the patient is already receiving the lowest possible tolerated dose, then consider discontinuing SOHONOS temporarily or permanently. Initiate subsequent flare-up dosing at the same reduced dose that was tolerated previously.

Table 2. Dose Reduction of SOHONOS for Flare-Up and Chronic Treatment
Dose Prescribed | Reduced Dose
20 mg | 15 mg
15 mg | 12.5 mg
12.5 mg | 10 mg
10 mg | 7.5 mg
7.5 mg | 5 mg
6 mg | 4 mg
5 mg | 2.5 mg
4 mg | 2 mg
3 mg | 1.5 mg
2.5 mg | 1 mg

2.5 Dosage Modifications for Drug Interactions

Moderate CYP3A Inhibitors:

Avoid concomitant use of a moderate CYP3A inhibitor, if possible. If concomitant use will occur, reduce the dose of SOHONOS by half as shown in Table 3 when co-administered with moderate CYP3A inhibitors [see Drug Interactions (7.1) and Clinical Pharmacology (12.3)].

Table 3. Dose Reduction of SOHONOS for Use with Moderate CYP3A Inhibitors
Weight | Daily Dosage | Week 1 to 4 Flare-up Dosage | Week 5 to 12 Flare-up Dosage
10 kg to 19.9 kg | 1 mg | 5 mg | 2.5 mg
20 kg to 39.9 kg | 1.5 mg | 6 mg | 3 mg
40 kg to 59.9 kg | 2 mg | 7.5 mg | 4 mg
≥ 60 kg [All pediatric patients ≥14 years of age and adults should receive the dose in the ≥60 kg weight category.] | 2.5 mg | 10 mg | 5 mg

3 DOSAGE FORMS AND STRENGTHS

SOHONOS is available in 5 strengths as an opaque white elongated size "0" hard-gelatin capsule, containing white to off-white powder. Table 4 shows capsules' strengths and imprints.

Table 4. SOHONOS Capsules' Strengths and Imprints
Strength (mg) | Imprint
1 | PVO 1
1.5 | PVO 1.5
2.5 | PVO 2.5
5 | PVO 5
10 | PVO 10

4 CONTRAINDICATIONS

SOHONOS is contraindicated in the following patients:

- During Pregnancy [see Warnings and Precautions (5.1) and Use in Specific Populations (8.1)].
- A history of allergy or hypersensitivity to retinoids, or to any component of SOHONOS. Anaphylaxis and other allergic reactions have occurred with other retinoids. [see Description (11)].

5 WARNINGS AND PRECAUTIONS

5.1 Embryo-Fetal Toxicity

SOHONOS can cause fetal harm and is contraindicated during pregnancy. SOHONOS is a member of the retinoid class of drugs which is associated with birth defects in humans. In animal reproduction studies, palovarotene administered orally to pregnant rats during organogenesis was teratogenic and caused fetal malformations typical of retinoids including cleft palate, misshapen skull bones, and shortening of the long bones at clinically relevant exposures.

For females of reproductive potential, verify that the patient is not pregnant prior to initiating treatment, periodically during the course of therapy and one month after treatment discontinuation. Advise females of reproductive potential to use an effective method of contraception at least one month prior to treatment, during treatment with SOHONOS and for 1 month after the last dose [see Use in Specific Populations (8.1, 8.3) and Clinical Pharmacology (12.3)]. If a pregnancy occurs during SOHONOS treatment, discontinue treatment immediately and refer the patient to an obstetrician/gynecologist experienced in reproductive toxicity for further evaluation and counseling.

Patients should be informed not to donate blood during SOHONOS therapy and for 1 week following discontinuation because the blood might be given to a pregnant patient whose fetus must not be exposed to palovarotene.

5.2 Premature Epiphyseal Closure in Growing Pediatric Patients

SOHONOS can cause irreversible premature epiphyseal closure and potential adverse effects on growth. In clinical studies, premature epiphyseal closure occurred with SOHONOS treatment in growing pediatric patients with FOP [see Adverse Reactions (6.1) and Use in Specific Populations (8.4)].

Monitoring of linear growth is recommended in growing pediatric patients [see Use in Specific Populations (8.4)]. Prior to starting treatment with SOHONOS, all growing pediatric patients should undergo baseline assessment of skeletal maturity via hand/wrist and knee x-rays, standard growth curves and pubertal staging. Continued monitoring is recommended every 6 to 12 months until patients reach skeletal maturity or final adult height.

If a patient exhibits signs of premature epiphyseal closure or adverse effects on growth based on clinical or radiologic evaluations, further evaluation may be required, including an assessment of the benefits and risks of continued treatment, or temporary or permanent discontinuation of SOHONOS until the patient achieves epiphyseal closure and skeletal maturity.

5.3 Mucocutaneous Adverse Reactions

Mucocutaneous adverse reactions including dry skin, lip dry, pruritus, rash, alopecia, erythema, skin exfoliation [skin peeling], and dry eye occurred in most (98%) patients treated with SOHONOS. SOHONOS may contribute to an increased risk of skin and soft tissue infections, particularly paronychia and decubitus ulcer, due to a decreased skin barrier from adverse reactions such as dry and peeling skin [see Adverse Reactions (6.1)]. Some of these mucocutaneous adverse reactions led to dose reductions which occurred more frequently during flare-up dosing suggesting a dose response relationship.

Prophylactic measures to minimize risk and/or treat the mucocutaneous adverse reactions are recommended (e.g., skin emollients, sunscreen, lip moisturizers, or artificial tears). Some patients may require dose reduction or drug discontinuation [see Dosage and Administration (2.4)].

Photosensitivity

Photosensitivity reactions, such as exaggerated sunburn reactions (e.g., burning, erythema, blistering) involving areas exposed to the sun have been associated with the use of retinoids and may occur with SOHONOS. Precautionary measures for phototoxicity are recommended. Excessive exposure to sun or artificial ultraviolet light should be avoided, and protection from sunlight should be used when exposure cannot be avoided (use of sunscreens, protective clothing, and use of sunglasses).

5.4 Metabolic Bone Disorders

Bone mineral density and fracture

Retinoids are associated with bone toxicity, including reductions in bone mass and spontaneous reports of osteoporosis and fracture. In FOP clinical trials, SOHONOS resulted in decreased vertebral bone mineral content and bone density, and an increased risk of radiologically observed vertebral (T4 to L4) fractures in treated adult and pediatric patients compared to untreated patients. Periodic radiological assessment of the spine is recommended. [see Adverse Reactions (6.1)].

Hyperostosis

Retinoids have been associated with hyperostotic changes (bone spurs) and calcification of tendons or ligaments and may occur with SOHONOS. These effects generally occur with long-term use, especially at high doses.

5.5 Psychiatric Disorders

New or worsening psychiatric events were reported with SOHONOS use. These include depression, anxiety, mood alterations and suicidal thoughts and behaviors. There is a relatively high background prevalence of psychiatric disorders in untreated patients with FOP. Monitor for development of new or worsening psychiatric symptoms during treatment with SOHONOS [see Adverse Reactions (6.1)]. Individuals with a history of psychiatric illness may be more susceptible to these adverse effects. Patients and/or caregivers should contact their healthcare provider if new or worsening psychiatric symptoms develop during treatment with SOHONOS.

5.6 Night Blindness

Night blindness has been associated with systemic retinoids, including SOHONOS. This may be dose-dependent, making driving a vehicle at night potentially hazardous during treatment. Night blindness is generally reversible after cessation of treatment but can also persist in some cases. Advise patients to be cautious when driving or operating any vehicle at night and to seek medical attention in the event of vision impairment.

6 ADVERSE REACTIONS

The following clinically significant adverse reactions are described elsewhere in the labeling:

- Premature Epiphyseal Closure in Growing Pediatric Patients [see Warnings and Precautions (5.2)]
- Mucocutaneous Adverse Reactions [see Warnings and Precautions (5.3)]
- Metabolic Bone Disorders [see Warnings and Precautions (5.4)]
- Psychiatric Disorders [see Warnings and Precautions (5.5)]
- Night Blindness [see Warnings and Precautions (5.6)]

6.1 Clinical Trials Experience

Because clinical trials are conducted under widely varying conditions, adverse reaction rates observed in the clinical trials of a drug cannot be directly compared to rates in the clinical trials of another drug and may not reflect the rates observed in practice.

The safety of SOHONOS was evaluated in clinical studies that enrolled a total of 164 subjects with FOP, including 139 subjects in the indicated population of ages 8 years and above for females and 10 years and above for males (8/10 years and older). Most of these subjects received open label treatment with the chronic daily/flare-up regimen, consisting of 5 mg daily dosage of oral SOHONOS with a 20/10 mg dosage as needed for 12 weeks at the time of flare-up (4 weeks of 20 mg once daily followed by 10 mg once daily for 8 weeks), with all doses reduced by weight in subjects who were less than 90% skeletally mature. The mean duration of exposure was 79 weeks for chronic dosing (N=131 subjects) and 35 weeks for flare-up dosing (N=105 subjects). The mean age of these subjects was 19 years (range 8 to 61 years); 51% were male.

Serious adverse reactions occurred in 21 (15%) SOHONOS treated subjects in the 8/10 years or older population with the most common serious adverse reaction being premature epiphyseal closure. Adverse reactions leading to permanent discontinuation occurred in 11 (8%) SOHONOS treated subjects with dry skin being the most common in 2 (1%) subjects. Mucocutaneous adverse reactions leading to dose reductions were more common during SOHONOS 20/10 mg flare-up treatment (37%) than during chronic treatment (4%).

Table 5 below presents adverse reactions which occurred in at least 10% of FOP subjects 8/10 years and older during treatment with chronic or flare-up dosing.

Table 5. Summary of Adverse Reactions Reported at greater than 10% Frequency in FOP Subjects 8/10 years and older in Clinical Trials
Adverse Reaction | Chronic 5 mg N=131 n (%) | Flare-up dosing 20/10 mg N=105 n (%)
Dry skin | 80 (61) | 60 (57)
Lip dry [includes lip dry, chapped lips, cheilitis] | 62 (47) | 40 (38)
Arthralgia | 47 (36) | 32 (31)
Pruritus [includes pruritus, pruritus generalized, and rash pruritic] | 45 (34) | 50 (48)
Pain in extremity | 38 (29) | 29 (28)
Rash [includes rash, rash generalized, rash maculo-papular] | 36 (28) | 31 (30)
Alopecia | 32 (24) | 31 (30)
Erythema [includes erythema, generalized erythema, flushing, rash erythematous] | 25 (19) | 34 (32)
Headache [includes headache and migraine] | 25 (19) | 20 (19)
Back pain [includes back pain, flank pain, sciatica] | 22 (17) | 12 (11)
Skin exfoliation [skin peeling] | 20 (15) | 30 (29)
Nausea | 20 (15) | 14 (13)
Musculoskeletal pain | 18 (14) | 14 (13)
Myalgia [includes myalgia, musculoskeletal discomfort] | 15 (12) | 9 (9)
Dry eye | 13 (10) | 23 (22)
Hypersensitivity [includes drug eruption, hypersensitivity, pruritus allergic, drug hypersensitivity] | 13 (10) | 21 (20)
Peripheral edema [includes peripheral swelling, edema peripheral] | 12 (9) | 20 (19)
Fatigue [includes fatigue, lethargy, asthenia, malaise] | 7 (5) | 12 (11)
Doses were reduced according to body weight in subjects who were less than 90% skeletally mature

Premature epiphyseal closure

Subjects under 18 years with open epiphyses were assessed for growth during the clinical studies. Premature epiphyseal closure was identified by scheduled imaging in 27% of subjects who were less than 18 years of age at enrollment and was more common in younger compared with older subjects (31% in subjects between 8/10 years to 14 years and no subjects 14 years or older). Many of the affected subjects exhibited slowing of growth in height. [see Use in Specific Populations (8.4) and Clinical Studies (14)].

Mucocutaneous Adverse Reactions

Mucocutaneous adverse reactions observed in over 10% of subjects (N=134) were dry skin (78%), lip dry (66%), pruritus (55%), alopecia (44%), rash (42%), erythema (37%), skin exfoliation [skin peeling] (31%), and skin irritation (11%). In addition, dry eye occurred in 25% of subjects.

Bone Mineral Density and Fractures

Loss of bone mineral density and radiological vertebral fractures (PT: Spinal fracture) were identified as a risk associated with SOHONOS based on novel analyses performed on whole body CT data in FOP subjects in the Phase 3 study [see Warnings and Precautions (5.4)].

Hepatotoxicity

Retinoids have been associated with dose dependent elevations of liver enzymes and isolated cases of severe hepatitis. In SOHONOS studies of FOP, elevated ALT was observed in 7.0% of subjects during 20/10 mg flare-up dosing and 1% of subjects during 5 mg chronic dosing. There were no subjects who required dose reduction or treatment discontinuation due to liver enzyme elevations.

Hypertriglyceridemia

Systemic retinoids may cause marked elevations of serum triglycerides. In FOP studies, hypertriglyceridemia was reported in 2 subjects during chronic SOHONOS treatment (2%) and in 4 subjects during flare-up dosing (4%).

Pancreatitis

Pancreatitis has been reported with other systemic retinoids, both with and without elevated triglycerides, including fatal cases. In palovarotene studies, one healthy subject developed acute pancreatitis, possibly related to concomitant use of ketoconazole in a drug-drug interaction study. There were no reports of pancreatitis in the FOP clinical studies.

Night Blindness

One reaction of night blindness was observed in SOHONOS treated subjects.

Intracranial Hypertension (Pseudotumor Cerebri)

Systemic retinoid use has been associated with cases of benign intracranial hypertension (also called pseudotumor cerebri), some of which involved the concomitant use of tetracyclines. There were no reports of benign intracranial hypertension in the FOP clinical studies [see Drug Interactions (7.3)].

7 DRUG INTERACTIONS

7.1 Effect of Other Drugs on SOHONOS

Clinically significant drug interactions affecting the exposure of SOHONOS are listed in Table 6.

Table 6. Drugs that affect exposure of SOHONOS.
Strong CYP3A Inhibitors
Clinical Impact | Co-administration of SOHONOS with strong CYP3A4 inhibitors increased the exposures of palovarotene [see Clinical Pharmacology (12.3)], which may increase the risk of SOHONOS adverse reactions.
Prevention or Management | Avoid concomitant use of a strong CYP3A4 inhibitor during SOHONOS treatment [see Dosage and Administration (2.5)].
Moderate CYP3A Inhibitors
Clinical Impact | Co-administration of SOHONOS with moderate CYP3A4 inhibitors may increase the exposure of palovarotene [see Clinical Pharmacology (12.3)], which may increase the risk of SOHONOS adverse reactions.
Prevention or Management | Avoid concomitant use of a moderate CYP3A4 inhibitor with SOHONOS, if possible. If co-administration will occur, reduce the SOHONOS dose by half when co-administered with moderate CYP3A inhibitors [see Dosage and Administration (2.5)].
Strong CYP3A Inducers
Clinical Impact | Co-administration of SOHONOS with strong CYP3A4 inducers decreased the exposure of palovarotene [see Clinical Pharmacology (12.3)], which may reduce the effectiveness of SOHONOS.
Prevention or Management | Avoid concomitant use of strong CYP3A4 inducers with SOHONOS. [see Dosage and Administration (2.5)].
Moderate CYP3A Inducers
Clinical Impact | Co-administration of moderate CYP3A4 inducers with palovarotene may decrease palovarotene exposure [see Clinical Pharmacology (12.3)], which may reduce the effectiveness of SOHONOS.
Prevention or Management | Avoid concomitant use of moderate CYP3A4 inducers with SOHONOS.

7.2 Vitamin A

Palovarotene belongs to the same pharmacological class as vitamin A. Therefore, the use of both vitamin A and SOHONOS at the same time may lead to additive effects. Concomitant administration of vitamin A in doses higher than the recommended daily allowance (RDA) and/or other oral retinoids with SOHONOS must be avoided because of the risk of hypervitaminosis A.

7.3 Tetracyclines

Systemic retinoid use has been associated with cases of benign intracranial hypertension (also called pseudotumor cerebri), some of which involved the concomitant use of tetracyclines. Avoid coadministration of SOHONOS with tetracycline derivatives [see Adverse Reactions (6.1)].

7.4 Systemic Corticosteroids

No clinically significant drug-drug interaction is expected when SOHONOS is co-administered with prednisone [see Clinical Pharmacology (12.3)].

8 USE IN SPECIFIC POPULATIONS

8.1 Pregnancy

Risk Summary

SOHONOS is contraindicated during pregnancy. Based on the findings in animal studies and class effects of retinoids, SOHONOS can cause fetal harm when administered during pregnancy [see Warnings and Precautions (5.1) and Use in Specific Populations (8.3)]. In animal reproduction studies, oral administration of palovarotene to pregnant rats during the period of organogenesis resulted in multiple fetal malformations typical of retinoids (e.g., cleft palate, malformed skull bone, shortening of the long bones) at doses ≥0.25 mg/kg/day (less than the clinical exposure) (see Data). There are no available human data on SOHONOS use in pregnant women. If pregnancy occurs during treatment with SOHONOS, discontinue treatment immediately and refer the patient to an obstetrician/gynecologist or other specialist experienced in reproductive toxicity for further evaluation and counseling.

Data

Animal Data

Palovarotene oral administration to pregnant rats during the period of organogenesis (gestation day 6 to 17) at doses of 0.01, 0.25 and 1.25 mg/kg/day resulted in fetal malformations consistent with retinoid-mediated embryopathy. Palovarotene exposure resulted in fetal external, visceral and skeletal malformations typical of retinoids, including defects in the mouth (cleft palate, protruding tongue), eye (anophthalmia, microphthalmia), skull (dilated cerebral ventricle, misshapen brain), skeleton (shortening of the long bones), blood vessels, kidney, and ureters at doses ≥ 0.25 mg/kg/day (less than the clinical exposure). The fetal toxicity was observed at maternal rat exposures well below the range of clinically relevant exposures.

8.2 Lactation

Risk Summary

There are no data available on the presence of palovarotene or its main metabolites in either animal or human milk, the effects on the breastfed infant, or on milk production. Because of the potential for serious adverse reactions in breastfed infants exposed to palovarotene through breastmilk, advise females that breastfeeding is not recommended during treatment with SOHONOS, and for at least 1 month after the final dose of SOHONOS.

8.3 Females and Males of Reproductive Potential

SOHONOS can cause fetal harm when administered during pregnancy [see Use in Specific Populations (8.1)]

Pregnancy Testing

Obtain a negative serum pregnancy test within one week prior to SOHONOS therapy. Verify that patient is not pregnant periodically, as needed, over the course of treatment with SOHONOS and one month after treatment discontinuation unless they are not at risk of pregnancy.

Contraception

Females

SOHONOS can cause embryo-fetal harm when administered during pregnancy [see Warnings and Precautions (5.1), Use in Specific Populations (8.1)]. Advise females of reproductive potential to use effective contraception at least one month prior to treatment, during treatment with SOHONOS and for 1 month after the last dose, unless continuous abstinence is chosen.

Males

Palovarotene is present in semen (0.7 ng/mL) in amounts 100-fold lower than the maternal plasma exposure at the no observed adverse effect level (NOAEL) for fetal toxicity observed in animal studies. Administration of SOHONOS to a male patient is considered unlikely to affect development of an embryo or fetus carried by a pregnant female sexual partner exposed to SOHONOS via the patient's semen.

8.4 Pediatric Use

The safety and effectiveness of SOHONOS for the treatment of FOP have been established in pediatric patients aged 8 years and older for females and 10 years and older for males. Use of SOHONOS for this indication is supported by evidence from clinical studies in adults and pediatric subjects [see Clinical Studies (14)]. The safety and effectiveness of SOHONOS for the treatment of FOP have not been established in pediatric patients less than 8 years of age in females and less than 10 years of age for males. SOHONOS is not recommended for use in patients younger than 8 years of age for females and 10 years of age for males because of the potential for premature epiphyseal closure. Clinical studies have shown that growing patients with open epiphyses are at risk of developing premature epiphyseal closure when treated with SOHONOS [see Warnings and Precautions (5.2), Adverse Reactions (6.1) and Clinical Studies (14.1)].

Bone Safety

In clinical studies with SOHONOS, assessments of growth and bone safety in growing children included linear and knee height, femur and tibia length measured by Whole-Body Computed Tomography (WBCT), and hand/wrist and knee radiographs. Premature epiphyseal closure has been identified as an irreversible serious risk associated with SOHONOS treatment. Premature epiphyseal closure was observed as early as 6 months after initiating therapy with the majority occurring at or after 12 months. In SOHONOS treated subjects there was a trend of declining height Z-scores in adolescent subjects, potentially due to a loss of linear height and/or increasing spinal deformity. The long-term effects on final height in subjects with FOP treated with SOHONOS have not been established. [see Adverse Reactions (6.1)].

Monitoring Recommendation

Prior to starting treatment with SOHONOS, all growing children should undergo baseline clinical and radiological assessments including but not limited to an assessment of skeletal maturity via hand/wrist and knee x-rays, standard growth curves and pubertal staging. Continued monitoring is recommended every 6-12 months until patients reach skeletal maturity (e.g., epiphyseal closure) or final adult height [see Warnings and Precautions (5.2)].

Juvenile Animal Data

A juvenile animal study was conducted in juvenile rats given daily oral doses of palovarotene at 0.1, 0.5 or 1.2 mg/kg/day from Week 3 to Week 9 of age (prior to epiphyseal fusion). Palovarotene adversely affected skeletal growth and development including, reduction in bone size, abnormal bone shape and/or geometry, diffuse bone loss, and growth in general were affected at ≥ 0.5 mg/kg/day (less than the clinical exposure). As expected, physes were either widened due to an expanded zone of cartilage hypertrophy/maturation (sometimes accompanied by chondrodysplasia), narrowed, or partially/completely closed. In the proximal femur, avascular necrosis of the femoral head was observed accompanied with malformations and microfractures of trabeculae in a few rats at 1.2 mg/kg/day (less than the clinical exposure). In vertebrae, palovarotene completely inhibited the endochondral ossification that normally occurs in the hyaline cartilage at the end of the vertebral body There also were tibial fractures in two high-dose females. The skeletal effects showed evidence of reversing after dosing discontinuation at 0.5 mg/kg/day, but not at highest dose of 1.2 mg/kg/day.

8.5 Geriatric Use

Clinical studies of SOHONOS did not include sufficient numbers of subjects aged 65 and over to determine whether they respond differently from younger subjects. Other reported clinical experience has not identified differences in responses between the elderly and younger patients. In general, dose selection for an elderly patient should be cautious, usually starting at the low end of the dosing range, reflecting the greater frequency of decreased hepatic, renal, or cardiac function, and of concomitant disease or other drug therapy.

8.6 Renal Impairment

The effect of renal impairment on the pharmacokinetics of palovarotene has not been evaluated. Given that palovarotene is hepatically eliminated, no dose adjustment of SOHONOS is recommended in patients with mild (CLcr 60 to 89 mL/min) or moderate (CLcr 30 to 59 mL/min) renal impairment. Use of SOHONOS in patients with severe (CLcr 15 to 29 mL/min) renal impairment is not recommended.

8.7 Hepatic Impairment

The effect of moderate or severe hepatic impairment on the pharmacokinetics of palovarotene has not been evaluated. SOHONOS undergoes extensive hepatic metabolism. No dose adjustment is recommended in patients with mild (Child-Pugh A) hepatic impairment. Use of SOHONOS in patients with moderate (Child-Pugh B) or severe (Child-Pugh C) hepatic impairment is not recommended.

10 OVERDOSAGE

No clinical experience with an overdose of SOHONOS has been reported. SOHONOS is a derivative of vitamin A. In case of accidental overdose, signs of hypervitaminosis A could appear, including severe headache, nausea or vomiting, drowsiness, irritability and pruritus. Any overdose should be treated with supportive care according to the signs and symptoms exhibited by the patient.

11 DESCRIPTION

Palovarotene is an orally bioavailable retinoid that acts as a retinoic acid receptor (RAR) agonist with particular selectivity at the gamma subtype of RAR. Palovarotene is chemically described as 4-[(E)-2-(5,5,8,8-tetramethyl-3-pyrazol-1-ylmethyl-5,6,7,8-tetrahydro-naphthalen-2-yl)-vinyl]-benzoic acid with an empirical formula of C27H30N2O2 and has a molecular weight of 414.54 g/mol.

The structural formula is represented below:

SOHONOS capsules are supplied in 1 mg, 1.5 mg, 2.5 mg, 5 mg and 10 mg strengths. Each capsule contains palovarotene as the active ingredient and the following inactive ingredients: croscarmellose sodium, lactose monohydrate, magnesium stearate, microcrystalline cellulose, povidone, and sodium lauryl sulfate. The capsule consists of gelatin and titanium dioxide. The black printing ink consists of black iron oxide, potassium hydroxide, propylene glycol and Shellac.

12 CLINICAL PHARMACOLOGY

12.1 Mechanism of Action

In patients with FOP, abnormal bone formation, including heterotopic ossification (HO), is driven by a gain-of-function mutation in the bone morphogenetic protein (BMP) type I receptor ALK2 (ACVR1). Palovarotene is an orally bioavailable retinoic acid receptor agonist, with particular selectivity at the gamma subtype of RAR. Through binding to RARγ, palovarotene decreases the BMP/ALK2 downstream signaling pathway by inhibiting the phosphorylation of SMAD1/5/8, which reduces ALK2/SMAD-dependent chondrogenesis and osteocyte differentiation resulting in reduced endochondral bone formation.

12.2 Pharmacodynamics

Cardiac Electrophysiology

At doses up to 2.5 times the maximum recommended dose, palovarotene does not prolong the QT interval to any clinically relevant extent.

12.3 Pharmacokinetics

Palovarotene exposure (AUC) increases proportionally from 0.02 to 50 mg (0.001 to 2.5 times the maximum recommended dosage). Steady-state is achieved by Day 3 following once daily dosing. Palovarotene exposure in patients with FOP are listed in Table 7.

Table 7. Palovarotene Exposures in Patients with FOP
Palovarotene Dosage | Cmax,ss (ng/mL) | AUC0-t (ng*h/mL) | Accumulation Ratio
Chronic dose 5 mg or weight-based equivalent | 40.6 (± 16.2) | 264 (± 98.4) | 1.16
Flare-up dose 10 mg or weight-based equivalent | 78.4 (± 33.3) | 540 (± 226) | 1.14
Flare-up dose 20 mg or weight-based equivalent | 165 (± 72.7) | 1060 (± 449) | 1.04
Pharmacokinetics parameters are presented as mean (± SD).

Absorption

The median time to achieve peak concentration (Tmax) of palovarotene was 3.0 to 4.0 hours across the chronic dose of 5 mg to flare-up dose of 10 and 20 mg.

Effect of Food

Palovarotene mean AUC and mean Cmax increased by approximately 40% and 16%, respectively; Tmax was delayed by approximately 2 hours with a high-fat, high-calorie meal (800 to 1000 calories, 15% protein, 25% carbohydrate, and 50 to 60% fat).

No clinically significant differences in the AUC and Cmax of palovarotene were observed when palovarotene was administered whole compared to the contents sprinkled onto one teaspoon of applesauce following a high-fat, high-caloric breakfast.

Distribution

The mean (SD) apparent volume of distribution (Vd/F) is 237 (± 90.1) L following administration of a single 20 mg dose with food. Protein binding of palovarotene is 97.9% to 99.6% in vitro.

The mean blood-to-plasma ratio of palovarotene in humans is 0.62.

Elimination

The mean elimination half-life is 8.7 hours following administration of a 20 mg once daily dosage for 14 days with a standard breakfast (800 to 1000 calories, 15% protein, 25% carbohydrate, and 50 to 60% fat). The apparent total body clearance (CL/F) of palovarotene is estimated at 19.9 L/h.

Metabolism

Palovarotene is extensively metabolized by CYP3A4 and to a minor extent by CYP2C8 and CYP2C19.

Following administration of [^14-C]-radiolabeled palovarotene, the contribution of palovarotene and its four known major metabolites (M2, M3, M4a, and M4b) represented collectively 40% of the total exposure in plasma. The pharmacological activity of M3 and M4b is approximately 1.7% and 4.2% of the activity of the parent drug.

Excretion

Following administration of a 1 mg dose of [^14C]-radiolabeled palovarotene in healthy subjects, 97.1% of the dose was recovered in the feces and 3.2% in the urine.

Specific Populations

There were no clinically significant differences in the pharmacokinetics of palovarotene based on age (2 to 85 years old), sex, race (Asian, black, white and others), smoking status, mild to moderate renal impairment, or mild hepatic impairment. The effect of severe renal impairment, or moderate to severe hepatic impairment on the pharmacokinetics of palovarotene is unknown.

Body Weight

Body weight (13 to 130 kg) was found to have a significant effect on the pharmacokinetics of palovarotene resulting in increasing exposure with decreasing weight at the same dose.

Pediatric Patients

The estimated steady-state AUC0-τ and Cmax,ss following weight-based dosing for 5, 10, and 20 mg (or dose equivalent) in pediatric patients <14 years old are comparable for the equivalent doses across the different weight groups.

Drug Interaction Studies

Clinical Studies and Model-Informed Approaches

Strong CYP3A Inhibitor: Co-administration of palovarotene with ketoconazole (strong CYP3A4 inhibitor) increased the Cmax and AUC of palovarotene by 2 and 3-fold, respectively.

Moderate CYP3A Inhibitor: Co-administration of palovarotene with erythromycin (moderate CYP3A4 inhibitor) increased the Cmax and AUC of palovarotene by 1.6 and 2.5-fold, respectively.

Strong CYP3A Inducer: Co-administration of palovarotene with rifampicin (strong CYP3A4 inducer) decrease the Cmax and AUC0-t of palovarotene by 19% and 11%, respectively.

Other Drugs: No clinically significant differences in the pharmacokinetics of palovarotene were observed when co-administered with prednisone 40 mg. No clinically significant differences in the pharmacokinetics of midazolam (CYP3A4 substrate) were observed when co-administered with palovarotene.

In Vitro Studies

Cytochrome P450 (CYP) Enzymes: Palovarotene is an inducer of CYP3A4 and CYP2B6, but not CYP1A2, CYP2C8, CYP2C9 and CYP2C19. Palovarotene is not an inhibitor of CYP1A2, CYP2B6, CYP2C8, CYP2C9, CYP2C19, CYP2D6 and CYP3A4.

Uridine diphosphate (UDP)-glucuronosyl transferase (UGT) Enzymes: Palovarotene is not an inhibitor or a substrate of UGT1A1, UGT1A3, UGT1A4, UGT1A6, UGT1A9 or UGT2B7.

Transporter Systems: Palovarotene is not an inhibitor of P-gp, OAT1, OAT3, OCT2, MATE1, MATE2 K, BCRP, OATP1B1, OATP1B3, OCT1, and BSEP. Palovarotene is not a substrate of P-gp, BCRP, OATP1B1, OATP1B3, or OCT1.

13 NONCLINICAL TOXICOLOGY

13.1 Carcinogenesis, Mutagenesis, Impairment of Fertility

Carcinogenesis and Mutagenesis

Long term studies to assess the carcinogenic potential of palovarotene have not been conducted.

Palovarotene and its metabolites were negative in the vitro bacterial reverse mutation (Ames) assay and an in vitro micronucleus assay in primary human lymphocyte. Palovarotene did not have any clastogenic effect in the in vivo mouse micronucleus study.

Impairment of Fertility

Palovarotene effects on fertility and reproductive function were assessed in male and female rats. In a female rat fertility study, palovarotene was orally administered to females for 14 days prior to mating with drug naïve males and up to GD 7 at the dose levels of 0.3, 1 and 3 mg/kg/day. Palovarotene caused prolonged periods of diestrous and reduced ovulation rate, resulting in lower numbers of implantation sites and live embryos at 3 mg/kg/day, a dose associated with maternal toxicity.

In a male rat fertility study, palovarotene was orally administered prior to mating, during mating, and up to scheduled euthanasia (approximately 11 weeks in total) at 0.3, 1 and 3 mg/kg/day. Palovarotene did not cause adverse effects on mating, fertility indices, conception rate, reproductive organ weights or sperm parameters up to 1 mg/kg/day (less than the clinical exposure). Males did not tolerate 3 mg/kg/day, as it produced severe systemic toxicity including deaths, adverse skin and hair coat clinical signs, and substantially reduced body weight.

14 CLINICAL STUDIES

14.1 Chronic/Flare-up Regimen

Study PVO-1A-301 (NCT03312634, Study 301) was a single arm study in 97 subjects with FOP with R206H mutation aged 4 years and older utilizing the Natural History Study (NHS, PVO-1A-001) as an external control (n=101). The primary efficacy endpoint was annualized volume of new heterotopic ossification (HO) as assessed by low-dose, whole body CT (WBCT) imaging (excluding head). All WBCT images from treated subjects in the 301 study and untreated subjects in the NHS were read in a manner blinded to study origination.

Study 301 subjects received SOHONOS 5 mg daily with increased dosing at the time of a flare-up defined as at least one symptom (e.g. pain, swelling, redness) consistent with a previous flare-up or a substantial high-risk traumatic event likely to lead to a flare-up, to 20 mg once daily for 4 weeks followed by 10 mg once daily for 8 weeks (denoted as the chronic/flare-up regimen), with flare-up treatment extension in 4-week increments for persistent symptoms. Anytime during flare-up treatment, the 12-week treatment restarted if the subject had another flare-up or substantial high-risk traumatic event. The dosing was adjusted according to body weight in skeletally immature children (children who had not reached at least 90% skeletal maturity defined as a bone age of ≥12 years 0 months for girls and ≥14 years 0 months for boys).

The mean age of subjects in the SOHONOS group (N=97) was 15.1 years; and 17.8 years in the untreated group (N=101). There were more male than female subjects in both the SOHONOS (53% and 47%, respectively) and untreated (55% and 45%, respectively) groups.

The mean annualized new HO was 9.4 cm^3/year in subjects receiving the chronic/flare-up SOHONOS treatment and 20.3 cm^3/year in untreated subjects in the NHS based on a linear mixed effect model. The treatment effect was about 10.9 cm^3/year with 95% confidence interval (-21.2 cm^3/year, -0.6 cm^3/year).

16 HOW SUPPLIED/STORAGE AND HANDLING

How Supplied

SOHONOS is an opaque white elongated hard-gelatin capsule. SOHONOS is available in size "0" capsule and supplied as a blister strip containing 14 capsules in a child resistant carton. Capsule contains white to off-white powder. Table 8 shows capsules' strengths, imprints, and NDC numbers.

Table 8. Capsules' Strengths, Imprints, and NDC numbers
Strength (mg) | Imprint | NDC
1 | PVO 1 | 15054-0010-1
1.5 | PVO 1.5 | 15054-0015-1
2.5 | PVO 2.5 | 15054-0025-1
5 | PVO 5 | 15054-0050-1
10 | PVO 10 | 15054-0100-1

Storage and Handling

This package is child-resistant. Keep out of reach of children. Store at 20° to 25°C (68° to 77°F); excursions permitted to 15° to 30°C (59° to 86°F) [See USP Controlled Room temperature]. SOHONOS must be kept in the original carton to protect from light.

SOHONOS capsules may be opened and the contents emptied on a teaspoon of soft food and taken immediately. If not taken immediately, it can be taken after a maximum of one hour after the sprinkling, provided it was maintained at room temperature and not exposed to direct sunlight.

17 PATIENT COUNSELING INFORMATION

Advise the patient and/or caregiver to read the FDA-approved patient labeling (Medication Guide).

Embryo-Fetal Toxicity:

Advise patients that SOHONOS can cause fetal harm and is contraindicated during pregnancy. Advise patients to verify that they are not pregnant prior to initiating and periodically during SOHONOS treatment as well as one month after treatment discontinuation [see Contraindications (4), Warnings and Precautions (5.1), and Use in Specific Populations (8.3)].

- Advise females of reproductive potential that they must avoid pregnancy while taking SOHONOS and for at least one month following discontinuation of therapy.
- Advise females of childbearing potential to use at least one highly effective method of contraception (i.e. IUD) or two effective methods (i.e. combined hormonal contraception in combination with another method of contraception such as a barrier method) during treatment with SOHONOS [see Use in Specific Populations (8.3)].
- Instruct patients to immediately stop taking SOHONOS if she becomes pregnant while taking SOHONOS and to rapidly consult her healthcare provider if there is a risk of pregnancy or if she might be pregnant.
- Instruct patients to not donate blood during SOHONOS treatment and for 1 week following discontinuation to avoid blood donation to a pregnant patient and fetus.

Lactation

Because of the potential for serious adverse reactions from SOHONOS in a breastfed child, advise females not to breastfeed during treatment with SOHONOS, and for at least 1 month after the last dose of SOHONOS.

Premature Epiphyseal Closure:

Inform patients that SOHONOS has been shown to cause premature epiphyseal closure in growing pediatric patients with FOP and discuss the proposed monitoring plan with the patient and caregiver [see Warnings and Precautions (5.2)].

Mucocutaneous Adverse Reactions:

Advise patients that they may experience dry skin, lip dry, pruritus, rash, alopecia, erythema, skin exfoliation, and dry eye. Discuss the plan to assess their symptoms and adjust the dose if needed [see Dosage and Administration (2.4) and Warning and Precautions (5.3)]. Recommend prophylactic measures to minimize risk and/or treat the mucocutaneous adverse reactions are recommended (e.g. skin emollients, sunscreen, lip moisturizers, artificial tears) [see Warnings and Precautions (5.3)].

Photosensitivity:

Advise patients of potential increased skin sensitivity to sunlight while taking SOHONOS and to minimize exposure to sunlight and artificial ultraviolet light [see Warnings and Precautions (5.3)].

Radiological Vertebral Fractures:

Inform patients that SOHONOS resulted in decreased vertebral bone mineral content, bone density and bone strength as well as an increased risk of radiologically observed vertebral fractures and that periodic radiological assessment of the spine is recommended [see Warnings and Precautions (5.4)].

Psychiatric Disorders:

Advise patients of the possibility of experiencing new or worsening psychiatric effects, including suicidal thoughts and behaviors, depression, depression aggravated, anxiety, and mood alterations. Particular care should be taken in patients with a history of psychiatric illness. Patients should be monitored for signs of depression and referred for appropriate treatment if necessary [see Warnings and Precautions (5.5)].

Night Blindness:

Advise patients of the risk of experiencing night blindness [see Warnings and Precautions (5.6)].

Drug Interactions:

Advise patients to inform their healthcare providers of all concomitant medications, including prescription medicines, over-the-counter drugs, and herbal products [see Dosage and Administration (2.5) and Drug Interactions (7)].

Dosing Instructions:

Advise the patient to take SOHONOS capsules with food. If the patient is unable to swallow the capsule, the capsule contents may be emptied onto soft food [see Dosage and Administration (2.3)].

Missed dose:

If a dose is missed, it should be taken as soon as the patient remembers. If the dose has been missed by more than 6 hours, advise the patient to skip the missed dose and continue with the next scheduled dose. Advise the patient to not take two doses at the same time or in the same day.

Distributed by: Ipsen Biopharmaceuticals, Inc. Cambridge, MA; 02142.

SOHONOS is a Registered trademark of Clementia Pharmaceuticals Inc.
©2025. Ipsen Biopharmaceuticals, Inc. All rights reserved.

MEDICATION GUIDE
SOHONOS [so-ho-nos]
(palovarotene)
capsules, for oral use

What is the most important information I should know about SOHONOS?

- SOHONOS can cause birth defects (deformed babies) if taken during pregnancy. Females who are pregnant or who plan to become pregnant must not take SOHONOS.
  Females who can become pregnant:
  - Your healthcare provider will ask you to take a pregnancy test 1 week before starting treatment with SOHONOS, periodically during treatment, and 1 month after you stop treatment with SOHONOS.
  - You must use effective birth control (contraception) starting at least 1 month before starting treatment with SOHONOS, during treatment and for 1 month after the last dose. Talk to your healthcare provider about birth control methods that may be right for you.
  - If you become pregnant or think you may be pregnant during treatment with SOHONOS, stop taking SOHONOS and call your healthcare provider right away.
  Because SOHONOS can cause birth defects, SOHONOS is only for people who can understand and agree to carry out all instructions for pregnancy prevention.
- SOHONOS can cause bone growth changes. Children may stop growing while taking SOHONOS. Bone growth changes such as permanent early closure of the growth plate in growing children have happened with SOHONOS. Your healthcare provider will closely monitor your child's bone growth and height during treatment with SOHONOS.

What is SOHONOS?

- SOHONOS is a prescription medicine used to reduce the amount of new heterotopic ossification in adults and children 8 years of age and older for females and 10 years of age and older for males with fibrodysplasia ossificans progressiva (FOP).
- SOHONOS is not recommended for females younger than 8 years of age or males younger than 10 years of age.

Do not take SOHONOS if you:

- are pregnant. (See "What is the most important information I should know about SOHONOS?")
- are allergic to medicines known as retinoids or any of the ingredients in SOHONOS. See the end of this Medication Guide for a complete list of ingredients in SOHONOS.

Before taking SOHONOS, tell your healthcare provider about all your medical conditions, including if you:

- have bone loss (osteoporosis), weak bones or any other bone problems.
- have or had mental health problems.
- have or have had kidney problems.
- have or have had liver problems.
- are breastfeeding or plan to breastfeed. It is not known if SOHONOS passes into your breastmilk. Breastfeeding is not recommended during treatment with SOHONOS and for at least 1 month after the last dose of SOHONOS. Talk to your healthcare provider about the best way to feed your baby if you take SOHONOS.

Tell your healthcare provider about all the medicines you take, including prescription and over-the-counter medicines, vitamins, and herbal supplements. SOHONOS and certain other medicines can interact with each other, sometimes causing serious side effects.

Know the medicines you take. Keep a list of them to show to your healthcare provider and pharmacist when you get a new medicine.

How should I take SOHONOS?

- Take SOHONOS exactly as your healthcare provider tells you.
- Take SOHONOS capsules whole with food. If you are unable to swallow the capsule, the capsule contents may be emptied onto a teaspoon (5 mL) of soft food (such as apple sauce, low-fat yogurt, or warm oatmeal) and taken within 1 hour of opening.
- Take SOHONOS at about the same time each day.
- Do not eat grapefruit or drink grapefruit juice during treatment with SOHONOS. Grapefruit may increase the levels of SOHONOS in your blood.
- If you miss a dose of SOHONOS, take it as soon as you remember. If the dose has been missed by more than 6 hours, the missed dose should be skipped, and next dose should be taken at the regular time. Do not take two doses at the same time or in the same day.
- Your healthcare provider may change your dose of SOHONOS as needed if you get certain side effects.
- If you take more SOHONOS than prescribed you may have symptoms such as severe headache, nausea or vomiting, drowsiness, irritability, and itching.

What should I avoid while taking SOHONOS?

- Do not get pregnant while taking SOHONOS. See "What is the most important Information I should know about SOHONOS?"
- Avoid excessive exposure to sunlight and ultraviolet lights (e.g., tanning machines). SOHONOS may make your skin more sensitive to sunlight and ultraviolet light and you may burn more easily. You should use sunscreen and wear sunglasses and protective clothing that covers your skin to help protect against sunburn if you must be in the sunlight during treatment with SOHONOS.
- Avoid driving at night until you know if SOHONOS has affected your vision. SOHONOS may decrease your ability to see in the dark.
- Do not donate blood while taking SOHONOS and for 1 week after stopping SOHONOS.

What are possible side effects of SOHONOS?

SOHONOS can cause serious side effects, including:

- See "What is the most important Information I should know about SOHONOS?"
- skin-related problems. SOHONOS may cause skin-related problems including dry skin, lips and eyes, hair loss, itching, redness, rash, and skin peeling. You may be at increased risk of developing skin and soft tissue infections while taking SOHONOS. If you develop these symptoms, your healthcare provider may tell you to use a moisturizer, sunscreen, or artificial tears.
- bone mineral density problems. SOHONOS can cause a reduction in bone mineral density (bone thinning) which can increase the risk of fractures in adults and children. Your healthcare provider should check you for this during treatment with SOHONOS.
- new or worsening mental health problems. SOHONOS may cause new or worsening mental health problems that include depression, anxiety, mood changes, and suicidal thoughts and behaviors. If you have a history of mental health problems, you may be at a higher risk of developing these side effects. Call your healthcare provider if you develop new or worsening mental health symptoms during treatment with SOHONOS. Your healthcare provider should monitor you for signs of depression and refer you for appropriate treatment, if necessary.
- vision problems. Decreased vision in the dark (night blindness). You may have difficulty seeing at night or in low lit areas. Your healthcare provider should send you to see an eye specialist if you experience vision problems.

The most common side effects of SOHONOS include:

- dry skin
- dry lips
- hair loss
- itching
- redness
- rash
- skin peeling
- drug eruption
- skin irritation

- swelling and small cracks in corner of the mouth
- nausea
- muscle and joint pain
- dry eyes
- headache
- fatigue

These are not all the possible side effects of SOHONOS. Call your doctor for medical advice about side effects. You may report side effects to FDA at 1-800-FDA-1088.

How should I store SOHONOS?

- Store SOHONOS at room temperature between 68° to 77°F (20° to 25°C) in the original carton to protect from light.
- Keep SOHONOS and all medicines out of the reach of children.

General information about the safe and effective use of SOHONOS

Medicines are sometimes prescribed for purposes other than those listed in a Medication Guide. Do not use SOHONOS for a condition for which it was not prescribed. Do not give SOHONOS to other people, even if they have the same symptoms that you have. It may harm them. You can ask your pharmacist or healthcare provider for information about SOHONOS that is written for healthcare professionals.

What are the ingredients in SOHONOS?

Active ingredient: palovarotene

Inactive ingredients: croscarmellose sodium, lactose monohydrate, magnesium stearate, microcrystalline cellulose, povidone, and sodium lauryl sulfate. The capsule consists of gelatin and titanium dioxide. The black printing ink consists of black iron oxide, potassium hydroxide, propylene glycol, and Shellac.

Distributed by:

Ipsen Biopharmaceuticals, Inc. Cambridge, MA; 02142.

For more information about SOHONOS, call 855-463-5127 or go to www.SOHONOS.com or drugsafety.USA@ipsen.com

SOHONOS is a Registered trademark of Clementia Pharmaceuticals Inc.

© 2025 Ipsen Biopharmaceuticals, Inc. All rights reserved.

This Medication Guide has been approved by the U.S. Food and Drug Administration

Revised: 3/2025

PRINCIPAL DISPLAY PANEL - 1 mg Capsule Blister Pack Carton

NDC 15054-0010-1
Rx Only

sohonos™
(palovarotene) capsules

1 mg
per capsule

For Oral Use
14 capsules

CAUSES BIRTH DEFECTS
DO NOT GET PREGNANT

LIFT OPEN HERE

PHARMACIST:
Dispense in the original
carton with the enclosed
Medication Guide.

IPSEN
Innovation for patient care

PRINCIPAL DISPLAY PANEL - 1.5 mg Capsule Blister Pack Carton

NDC 15054-0015-1
Rx Only

sohonos™
(palovarotene) capsules

1.5 mg
per capsule

For Oral Use
14 capsules

CAUSES BIRTH DEFECTS
DO NOT GET PREGNANT

LIFT OPEN HERE

PHARMACIST:
Dispense in the original
carton with the enclosed
Medication Guide.

IPSEN
Innovation for patient care

PRINCIPAL DISPLAY PANEL - 2.5 mg Capsule Blister Pack Carton

NDC 15054-0025-1
Rx Only

sohonos™
(palovarotene) capsules

2.5 mg
per capsule

For Oral Use
14 capsules

CAUSES BIRTH DEFECTS
DO NOT GET PREGNANT

LIFT OPEN HERE

PHARMACIST:
Dispense in the original
carton with the enclosed
Medication Guide.

IPSEN
Innovation for patient care

PRINCIPAL DISPLAY PANEL - 5 mg Capsule Blister Pack Carton

NDC 15054-0050-1
Rx Only

sohonos™
(palovarotene) capsules

5 mg
per capsule

For Oral Use
14 capsules

CAUSES BIRTH DEFECTS
DO NOT GET PREGNANT

LIFT OPEN HERE

PHARMACIST:
Dispense in the original
carton with the enclosed
Medication Guide.

IPSEN
Innovation for patient care

PRINCIPAL DISPLAY PANEL - 10 mg Capsule Blister Pack Carton

NDC 15054-0100-1
Rx Only

sohonos™
(palovarotene) capsules

10 mg
per capsule

For Oral Use
14 capsules

CAUSES BIRTH DEFECTS
DO NOT GET PREGNANT

LIFT OPEN HERE

PHARMACIST:
Dispense in the original
carton with the enclosed
Medication Guide.

IPSEN
Innovation for patient care